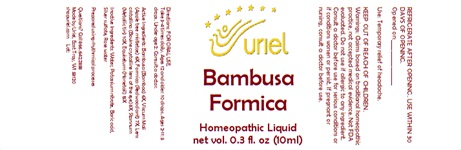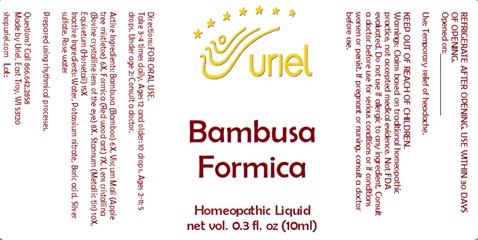 DRUG LABEL: Bambusa Formica
NDC: 48951-2134 | Form: LIQUID
Manufacturer: Uriel Pharmacy Inc.
Category: homeopathic | Type: HUMAN OTC DRUG LABEL
Date: 20241008

ACTIVE INGREDIENTS: BAMBUSA VULGARIS WHOLE 6 [hp_X]/1 mL; VISCUM ALBUM FRUITING TOP 6 [hp_X]/1 mL; FORMICA RUFA 7 [hp_X]/1 mL; TIN 10 [hp_X]/1 mL; EQUISETUM ARVENSE TOP 15 [hp_X]/1 mL; BOS TAURUS EYE 8 [hp_X]/1 mL
INACTIVE INGREDIENTS: ROSEMARY OIL; SILVER SULFATE; WATER; BORIC ACID; POTASSIUM NITRATE

Bambusa Formica

INDICATIONS AND USAGE

Directions: FOR ORAL USE.

DOSAGE AND ADMINISTRATION

Take 3-4 times daily. Ages 12 and older: 10 drops. Ages 2-11: 5 drops. Under age 2: Consult a doctor.

ACTIVE INGREDIENT

Active Ingredients: Bambusa (Bamboo) 6X, Viscum Mali (Apple tree mistletoe) 6X, Formica (Red wood ant) 7X, Lens cristallina (Bovine crystalline lens of the eye) 8X, Stannum (Metallic tin) 10X, Equisetum (Horsetail) 15X

INACTIVE INGREDIENT

Inactive Ingredients: Water, Potassium nitrate, Boric acid, Silver sulfate, Rose water

Prepared using rhythmical processes

PURPOSE

Use: Temporary relief of headache.

KEEP OUT OF REACH OF CHILDREN.

WARNINGS

Warnings: Claims based on traditional homeopathic practice, not accepted medical evidence. Not FDA evaluated. Do not use if allergic to any ingredient. Consult a doctor before use for serious conditions or if conditions worsen or persist.If pregnant or nursing, consult a doctor before use.Do not use if safety seal is broken or missing.

REFRIGERATE AFTER OPENING. USE WITHIN 30 DAYS OF OPENING.
Opened on:_________________

Questions? Call 866.642.2858
Made by Uriel, East Troy, WI 53120
shopuriel.com

Lot: